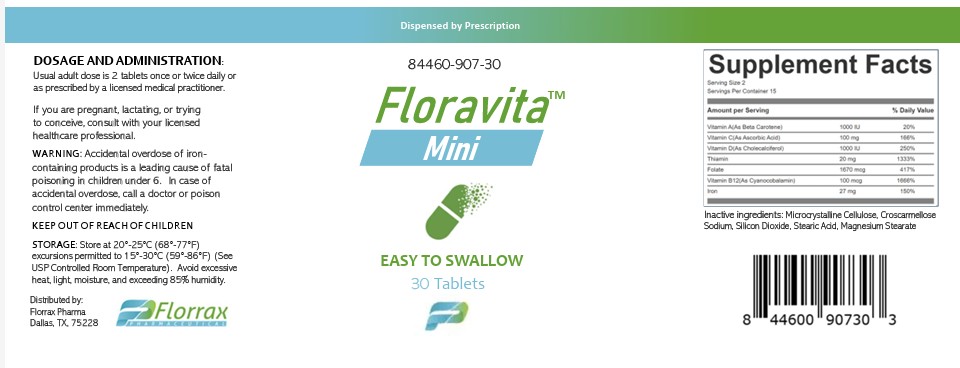 DRUG LABEL: Floravita Mini
NDC: 84460-907 | Form: TABLET
Manufacturer: Florrax Pharmaceutical
Category: prescription | Type: HUMAN PRESCRIPTION DRUG LABEL
Date: 20260212

ACTIVE INGREDIENTS: VITAMIN A 1000 [iU]/1 1; ASCORBIC ACID 100 mg/1 1; CHOLECALCIFEROL 1000 [iU]/1 1; THIAMINE 20 mg/1 1; FOLIC ACID 1.67 mg/1 1; CYANOCOBALAMIN 100 ug/1 1; FERROUS FUMARATE 27 mg/1 1
INACTIVE INGREDIENTS: MICROCRYSTALLINE CELLULOSE; CROSCARMELLOSE SODIUM; STEARIC ACID; MAGNESIUM STEARATE

Floravita Mini

DESCRIPTION

Floravita Mini is a prescription multivitamin/multimineral dietary supplement.

INDICATIONS AND USAGE

Floravite Mini is a prescription multivitamin/multi-mineral dietary supplement formulated for the clinical dietary management of a suboptimal nutritional status in patients where advanced folate, vitamin B supplementation, and maintenance of good health is needed.

WARNINGS

Accidental overdose of iron-containing products is a leading cause of fatal poising in children under 6. KEEP THIS PRODUCT OUT OF REACH OF CHILDREN. In the case of accidental overdose, call a doctor or poison control center immediately.

ADVERSE REACTIONS

Allergic sensitization has been reported following both oral and parenteral administration of folic acid. You should call your doctor for medical advice about serious adverse events. To reports adverse side effects or to obtain product information, contact Florrax Pharma at 888-321-2821.

DOSAGE AND ADMINISTRATION

Usual adult dose is 2 tablets by mouth once or twice daily as prescribed by a licensed medical practitioner.

HOW SUPPLIED

Bottles of 30 Tablets (84460-907-30). Tablet is tan, oval.

PRINCIPAL DISPLAY PANEL

pdp